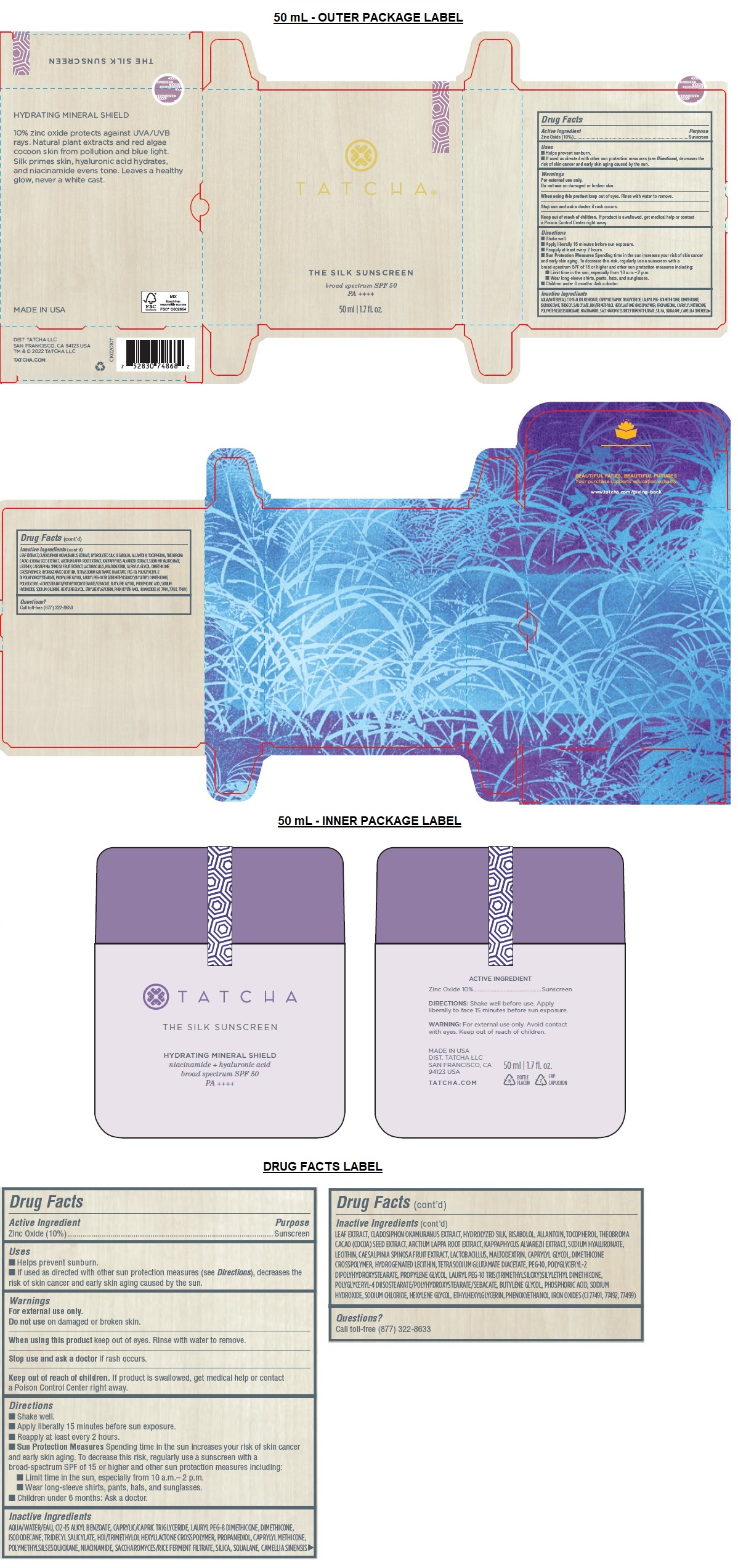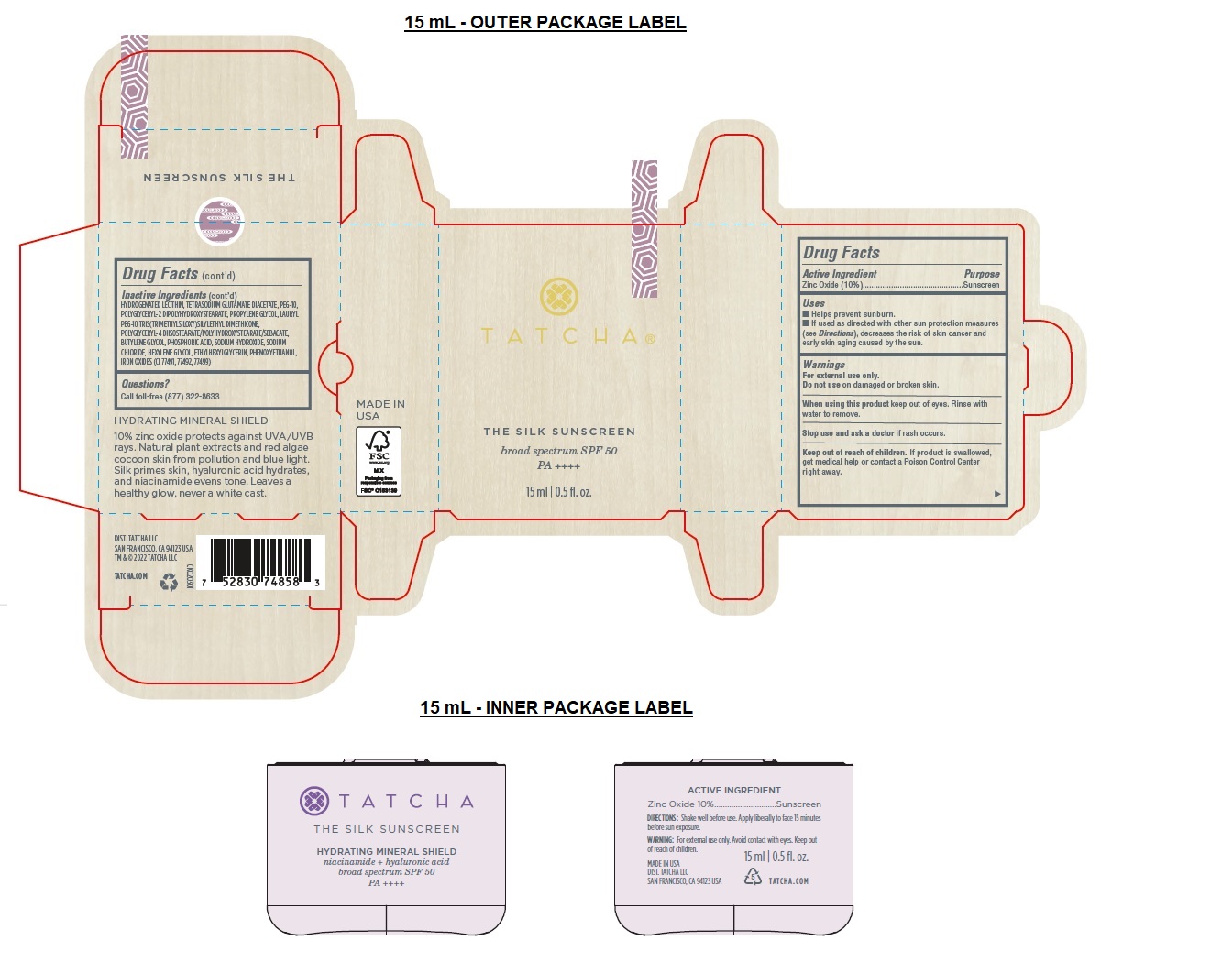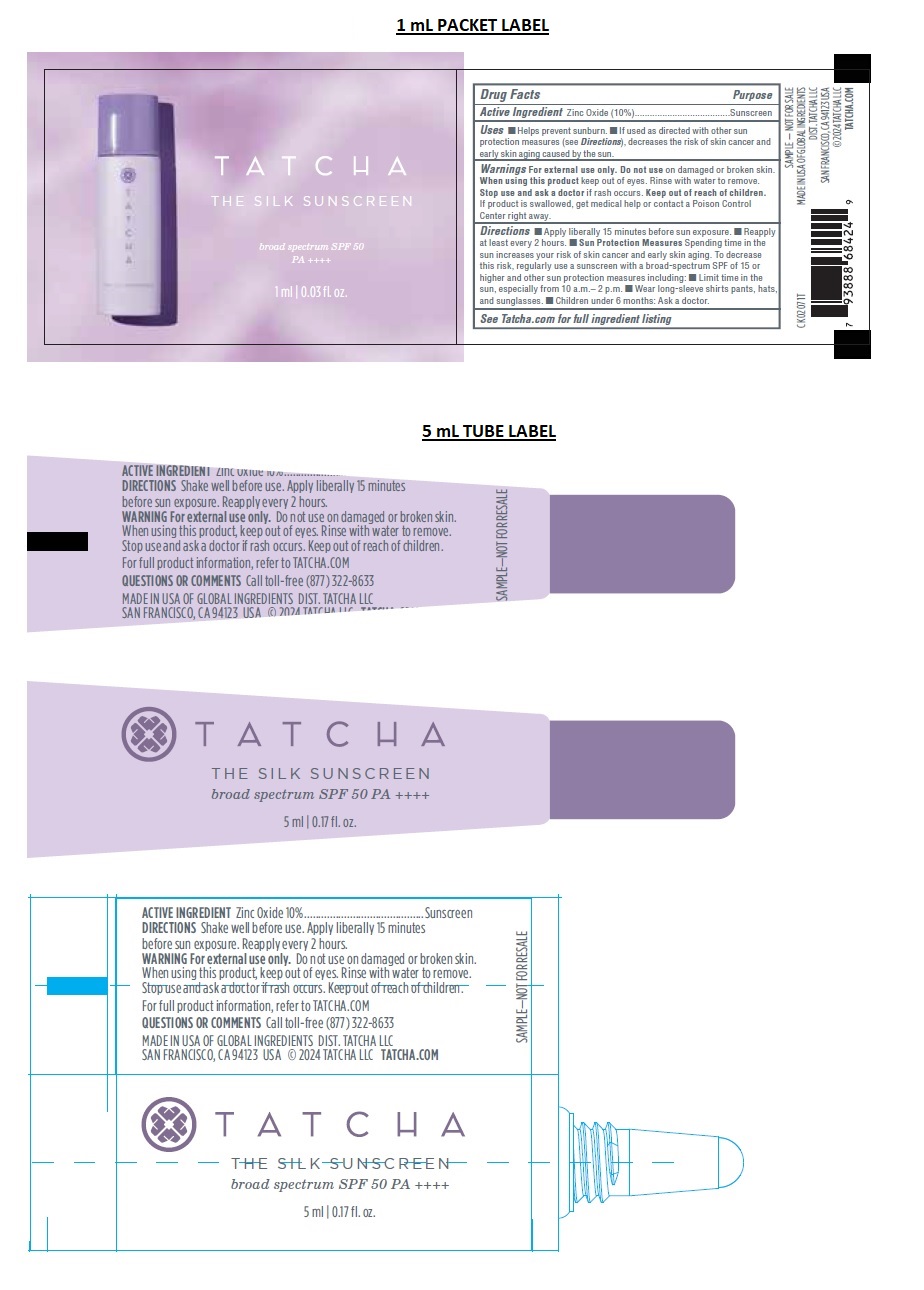 DRUG LABEL: TATCHA THE SILK SUNSCREEN
NDC: 69417-130 | Form: LOTION
Manufacturer: TATCHA INC.
Category: otc | Type: HUMAN OTC DRUG LABEL
Date: 20250331

ACTIVE INGREDIENTS: ZINC OXIDE 100 mg/1 mL
INACTIVE INGREDIENTS: WATER; ALKYL (C12-15) BENZOATE; MEDIUM-CHAIN TRIGLYCERIDES; LAURYL PEG-8 DIMETHICONE (300 CPS); DIMETHICONE, UNSPECIFIED; ISODODECANE; TRIDECYL SALICYLATE; HEXAMETHYLENE DIISOCYANATE/TRIMETHYLOL HEXYLLACTONE CROSSPOLYMER; PROPANEDIOL; CAPRYLYL TRISILOXANE; POLYMETHYLSILSESQUIOXANE (4.5 MICRONS); NIACINAMIDE; SILICON DIOXIDE; SQUALANE; GREEN TEA LEAF; CLADOSIPHON OKAMURANUS WHOLE; SILK, BASE HYDROLYZED (1000 MW); LEVOMENOL; ALLANTOIN; TOCOPHEROL; COCOA; ARCTIUM LAPPA ROOT; KAPPAPHYCUS ALVAREZII; HYALURONATE SODIUM; SOYBEAN LECITHIN; TARA SPINOSA FRUIT; BIFIDOBACTERIUM ANIMALIS LACTIS; MALTODEXTRIN; CAPRYLYL GLYCOL; DIMETHICONE CROSSPOLYMER; HYDROGENATED SOYBEAN LECITHIN; TETRASODIUM GLUTAMATE DIACETATE; POLYETHYLENE GLYCOL 500; POLYGLYCERYL-2 DIPOLYHYDROXYSTEARATE; PROPYLENE GLYCOL; POLYGLYCERYL-4 DIISOSTEARATE/POLYHYDROXYSTEARATE/SEBACATE; BUTYLENE GLYCOL; PHOSPHORIC ACID; SODIUM HYDROXIDE; SODIUM CHLORIDE; HEXYLENE GLYCOL; ETHYLHEXYLGLYCERIN; PHENOXYETHANOL; FERRIC OXIDE RED; FERRIC OXIDE YELLOW; FERROSOFERRIC OXIDE

TATCHA® THE SILK SUNSCREEN

Active Ingredient

Zinc Oxide (10%)

Purpose

Sunscreen

Uses

• Helps prevent sunburn.
• If used as directed with other sun protection measures (see Directions), decreases the risk of skin cancer and early skin aging caused by the sun.

Warnings

For external use only.

Do not use on damaged or broken skin.

When using this product keep out of eyes. Rinse with water to remove.

Stop use and ask a doctor if rash occurs.

Keep out of reach of children. If product is swallowed, get medical help or contact a Poison Control Center right away.

Directions

• Shake well before use.
• Apply liberally 15 minutes before sun exposure.
• Reapply at least every 2 hours.
• Sun Protection Measures Spending time in the sun increases your risk of skin cancer and early skin aging. To decrease this risk, regularly use a sunscreen with a broad-spectrum SPF of 15 or higher and other sun protection measures including:
• Limit time in the sun, especially from 10 a.m.– 2 p.m.
• Wear long-sleeve shirts, pants, hats, and sunglasses.
• Children under 6 months: Ask a doctor.

Inactive Ingredients

AQUA/WATER/EAU, C12-15 ALKYL BENZOATE, CAPRYLIC/CAPRIC TRIGLYCERIDE, LAURYL PEG-8 DIMETHICONE, DIMETHICONE, ISODODECANE, TRIDECYL SALICYLATE, HDI/TRIMETHYLOL HEXYLLACTONE CROSSPOLYMER, PROPANEDIOL, CAPRYLYL METHICONE, POLYMETHYLSILSESQUIOXANE, NIACINAMIDE, SACCHAROMYCES/RICE FERMENT FILTRATE, SILICA, SQUALANE, CAMELLIA SINENSIS LEAF EXTRACT, CLADOSIPHON OKAMURANUS EXTRACT, HYDROLYZED SILK, BISABOLOL, ALLANTOIN, TOCOPHEROL, THEOBROMA CACAO (COCOA) SEED EXTRACT, ARCTIUM LAPPA ROOT EXTRACT, KAPPAPHYCUS ALVAREZII EXTRACT, SODIUM HYALURONATE, LECITHIN, CAESALPINIA SPINOSA FRUIT EXTRACT, LACTOBACILLUS, MALTODEXTRIN, CAPRYLYL GLYCOL, DIMETHICONE CROSSPOLYMER, HYDROGENATED LECITHIN, TETRASODIUM GLUTAMATE DIACETATE, PEG-10, POLYGLYCERYL-2 DIPOLYHYDROXYSTEARATE, PROPYLENE GLYCOL, LAURYL PEG-10 TRIS(TRIMETHYLSILOXY)SILYLETHYL DIMETHICONE, POLYGLYCERYL-4 DIISOSTEARATE/POLYHYDROXYSTEARATE/SEBACATE, BUTYLENE GLYCOL, PHOSPHORIC ACID, SODIUM HYDROXIDE, SODIUM CHLORIDE, HEXYLENE GLYCOL, ETHYLHEXYLGLYCERIN, PHENOXYETHANOL, IRON OXIDES (CI 77491, 77492, 77499)

Questions?

Call toll-free (877) 322-8633

broad spectrum SPF 50

PA ++++

HYDRATING MINERAL SHIELD

10% zinc oxide protects against UVA/UVB rays. Natural plant extracts and red algae cocoon skin from pollution and blue light. Silk primes skin, hyaluronic acid hydrates, and niacinamide evens tone. Leaves a healthy glow, never a white cast.

BEAUTIFUL FACES, BEAUTIFUL FUTURES
Your purchase supports education equality

www.tatcha.com/giving-back

MADE IN USA

DIST. TATCHA LLC
SAN FRANCISCO, CA 94123 USA
TM & © 2022 TATCHA LLC

TATCHA.COM